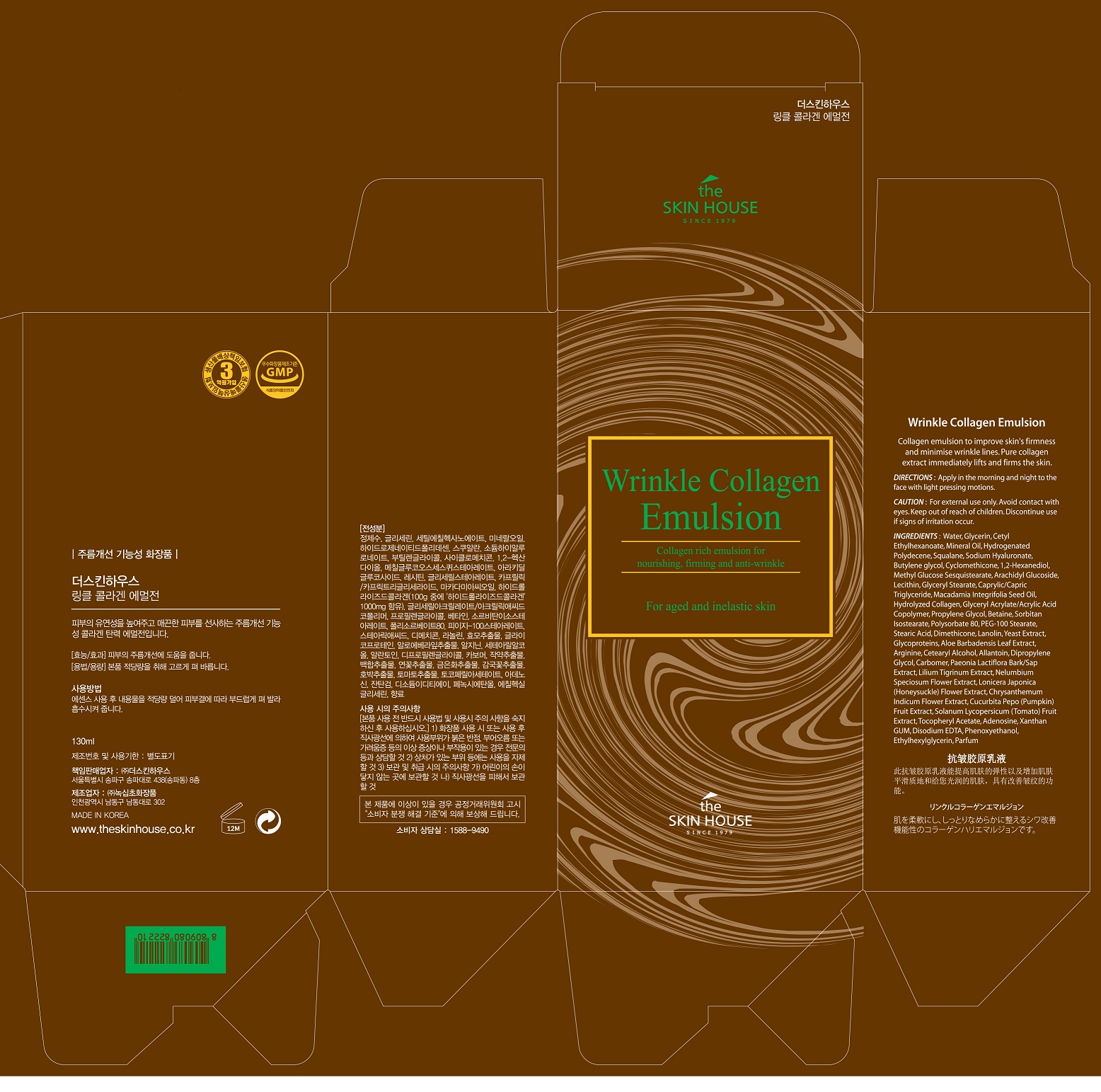 DRUG LABEL: THE SKIN HOUSE Wrinkle CollagenEmulsion
NDC: 73590-0031 | Form: EMULSION
Manufacturer: NOKSIBCHO cosmetic Co., Ltd.
Category: otc | Type: HUMAN OTC DRUG LABEL
Date: 20200330

ACTIVE INGREDIENTS: ADENOSINE 0.04 g/100 mL
INACTIVE INGREDIENTS: WATER

Drug Facts

ACTIVE INGREDIENT

adenosine

INACTIVE INGREDIENT

Water
Glycerin
Cetyl Ethylhexanoate
Mineral Oil
Hydrogenated Polydecene
Squalane
Sodium Hyaluronate
Butylene glycol
Cyclomethicone
1,2-Hexanediol
Methyl Glucose Sesquistearate
Arachidyl Glucoside
Lecithin
Glyceryl Stearate
Caprylic/Capric Triglyceride
Macadamia Integrifolia Seed Oil
Hydrolyzed Collagen
Glyceryl Acrylate/Acrylic Acid Copolymer
Propylene Glycol
Betaine
Sorbitan Isostearate
Polysorbate 80
PEG-100 Stearate
Stearic Acid
Dimethicone
Lanolin
Water
Glycoproteins
Aloe Barbadensis Leaf Extract
Arginine
Cetearyl Alcohol
Allantoin
Dipropylene Glycol
Carbomer
Paeonia Lactiflora Bark/Sap Extract
Lilium Tigrinum Extract
Nelumbium Speciosum Flower Extract
Lonicera Japonica (Honeysuckle) Flower Extract
Chrysanthemum Indicum Flower Extract
Cucurbita Pepo (Pumpkin) Fruit Extract
Solanum Lycopersicum (Tomato) Fruit Extract
Tocopheryl Acetate
Xanthan GUM
Disodium EDTA
Phenoxyethanol
Ethylhexylglycerin
Parfum

PURPOSE

wrinkle care

keep out of reach of the children

INDICATIONS AND USAGE

apply proper amount to the skin

WARNINGS

For external use only
When using this product

■ if the following symptoms occurs after use, stop use and consult with a skin specialist

red specks, swelling, itching

■ don’t use on the part where there is injury, eczema, or dermatitis

Keep out of reach of children

■ if swallowed, get medical help or contact a person control center immediately